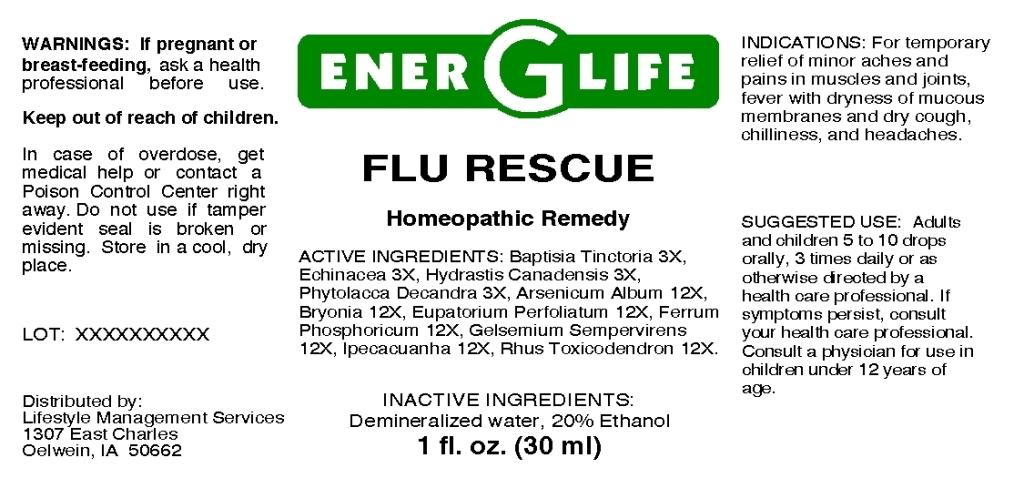 DRUG LABEL: Flu Rescue
NDC: 57520-0661 | Form: LIQUID
Manufacturer: Apotheca Company
Category: homeopathic | Type: HUMAN OTC DRUG LABEL
Date: 20110405

ACTIVE INGREDIENTS: BAPTISIA TINCTORIA ROOT 3 [hp_X]/1 mL; ECHINACEA 3 [hp_X]/1 mL; GOLDENSEAL 3 [hp_X]/1 mL; PHYTOLACCA AMERICANA ROOT 3 [hp_X]/1 mL; ARSENIC TRIOXIDE 12 [hp_X]/1 mL; BRYONIA ALBA ROOT 12 [hp_X]/1 mL; EUPATORIUM PERFOLIATUM FLOWERING TOP 12 [hp_X]/1 mL; FERRUM PHOSPHORICUM 12 [hp_X]/1 mL; GELSEMIUM SEMPERVIRENS ROOT 12 [hp_X]/1 mL; IPECAC 12 [hp_X]/1 mL; TOXICODENDRON PUBESCENS LEAF 12 [hp_X]/1 mL
INACTIVE INGREDIENTS: WATER; ALCOHOL

Flu Rescue

ACTIVE INGREDIENT

ACTIVE INGREDIENTS: Baptisia tinctoria 3X, Echinacea 3X, Hydrastis canadensis 3X, Phytolacca decandra 3X, Arsenicum album 12X, Bryonia 12X, Eupatorium perfoliatum 12X, Ferrum phosphoricum 12X, Gelsemium sempervirens 12X, Ipecacuanha 12X, Rhus toxicodendron 12X.

PURPOSE

INDICATIONS: For temporary relief of minor aches and pains in muscles and joints, fever with dryness of mucous membranes and dry cough, chilliness, and headaches.

WARNINGS

WARNINGS: If pregnant or breast-feeding, ask a health professional before use.

Keep out of reach of children. In case of overdose, get medical help or contact a Poison Control Center right away.

Do not use if tamper evident seal is broken or missing. Store in a cool, dry place.

DOSAGE AND ADMINISTRATION

SUGGESTED USE: Adults and children 5 to 10 drops orally, 3 times daily or as otherwise directed by a health care professional. If symptoms persist, consult your health care professional. Consult a physician for use in children under 12 years of age.

INACTIVE INGREDIENTS: Demineralized water, 20% Ethanol.

KEEP OUT OF REACH OF CHILDREN. In case of overdose, get medical help or contact a Poison Control Center right away.

INDICATIONS AND USAGE

INDICATIONS: For temporary relief of minor aches and pains in muscles and joints, fever with dryness of mucous membranes and dry cough, chilliness, and headaches.

QUESTIONS

Distributed by:

Lifestyla Management Services

1307 East Charles

Oelwein, IA 50662

PACKAGE LABEL

ENER G LIFE

FLU RESCUE

Homeopathic Remedy

1 fl. oz. (30 ml)